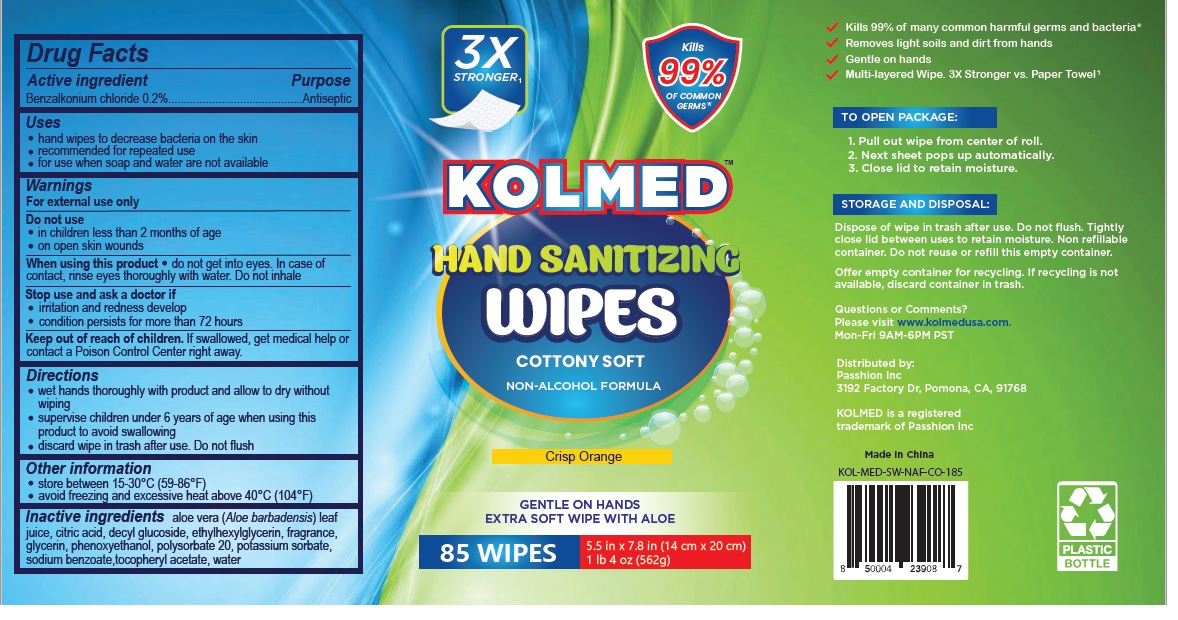 DRUG LABEL: KOLMED HAND SANITIZING WIPES
NDC: 75670-008 | Form: CLOTH
Manufacturer: SHANGHAI SANJUN GENERAL MERCHANDISE CO., LTD.
Category: otc | Type: HUMAN OTC DRUG LABEL
Date: 20200918

ACTIVE INGREDIENTS: BENZALKONIUM CHLORIDE 0.2 g/100 g
INACTIVE INGREDIENTS: ALOE VERA LEAF; CITRIC ACID MONOHYDRATE; DECYL GLUCOSIDE; ETHYLHEXYLGLYCERIN; GLYCERIN; PHENOXYETHANOL; POLYSORBATE 20; POTASSIUM SORBATE; SODIUM BENZOATE; .ALPHA.-TOCOPHEROL ACETATE; WATER

KOLMED HAND SANITIZING WIPES

Active ingredient

Benzalkonium chloride 0.2%

Purpose

Antiseptic

Uses

• hand wipes to decrease bacteria on the skin

• recommended for repeated use

• for use when soap and water are not available

Warnings

For external use only

Do not use

• in children less than 2 months of age

• on open skin wounds

When using this product • do not get into eyes. In case of contact, rinse eyes thoroughly with water. Do not inhale

Stop use and ask a doctor if

• irritation and redness develop

• condition persists for more than 72 hours

Keep out of reach of children. If swallowed, get medical help or contact a Poison Control Center right away.

Directions

• wet hands thoroughly with product and allow to dry without wiping

• supervise children under 6 years of age when using this product to avoid swallowing

• discard wipe in trash after use. Do not flush

Other information

• store between 15-30°C (59-86°F)

• avoid freezing and excessive heat above 40°C (104°F)

INACTIVE INGREDIENT

Inactive ingredients aloe vera (Aloe barbadensis) leaf juice, citric acid, decyl glucoside, ethylhexylglycerin,

fragrance, glycerin, phenoxyethanol, polysorbate 20, potassium sorbate, sodium benzoate,tocopheryl acetate, water

3X STRONGER

Kills 99% OF COMMON GERMS*

COTTONY SOFT

NON-ALCOHOL FORMULA

Crisp Orange

GENTLE ON HANDS

EXTRA SOFT WIPE WITH ALOE

√ Kills 99% of many common harmful germs and bacteria*

√ Removes light soils and dirt from hands

√ Gentle on hands

√ Multi-layered Wipe. 3X Stronger vs. Paper Towel^1

TO OPEN PACKAGE:

1. Pull out wipe from center of roll.

2. Next sheet pops up automatically.

3. Close lid to retain moisture.

STORAGE AND DISPOSAL:

Dispose of wipe in trash after use. Do not flush. Tightly close lid between uses to retain moisture.

Non refillable container. Do not reuse or refill this empty container.

Offer empty container for recycling. If recycling is not available, discard container in trash.

Questions or Comments?

Please visit www.kolmedusa.com.

Mon-Fri 9AM-6PM PST

Distributed by:

Passhion Inc

3192 Factory Dr, Pomona, CA, 91768

KOLMED is a registered trademark of Passhion Inc

Made in China